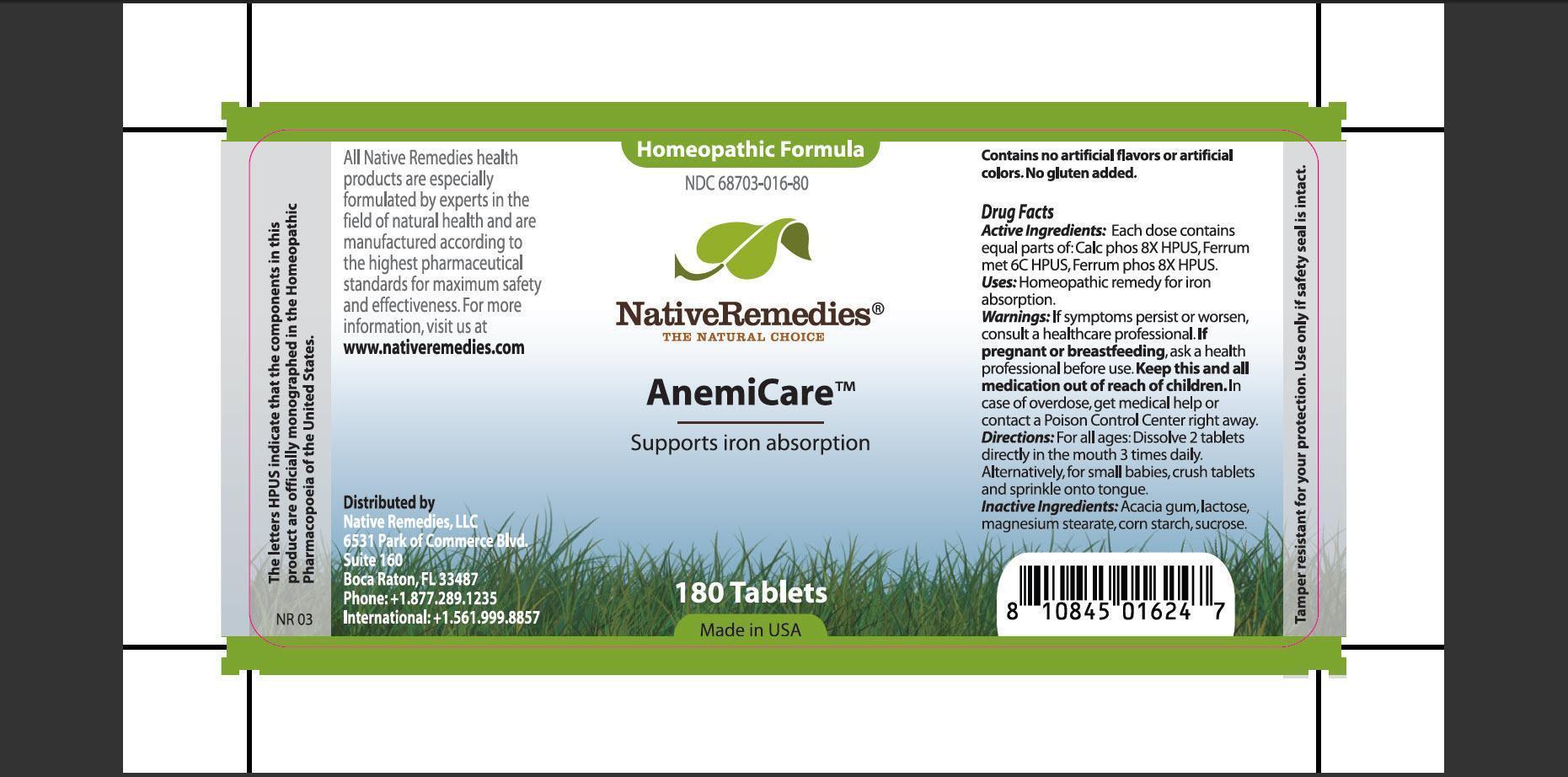 DRUG LABEL: AnemiCare
                
                
NDC: 68703-016 | Form: TABLET
Manufacturer: Native Remedies, LLC
Category: homeopathic | Type: HUMAN OTC DRUG LABEL
Date: 20130115

ACTIVE INGREDIENTS: TRIBASIC CALCIUM PHOSPHATE 8 [hp_X]/1 1; IRON 6 [hp_C]/1 1; FERROSOFERRIC PHOSPHATE 8 [hp_X]/1 1
INACTIVE INGREDIENTS: ACACIA; LACTOSE; MAGNESIUM STEARATE; STARCH, CORN; SUCROSE

AnemiCare

PURPOSE

Supports iron absorption

ACTIVE INGREDIENT

Active Ingredients: Each dose contains equal parts of: Calc phos 8X HPUS, Ferrum met 6C HPUS, Ferrum phos 8X HPUS.

INDICATIONS AND USAGE

Uses: Homeopathic remedy for iron absorption.

WARNINGS

Warnings: If symptoms persist or worsen, consult a healthcare professional.

PREGNANCY OR BREAST FEEDING

If pregnant or breastfeeding, as a health professional before use.

KEEP OUT OF REACH OF CHILDREN

Keep this and all medication out of reach of children.

OVERDOSAGE

In case of overdose, get medical help or contact a Poison Control Center right away.

DOSAGE AND ADMINISTRATION

Directions: For all ages: Dissolve 2 tablets directly in the mouth 3 times daily. Alternatively, for small babies, crush tablets and sprinkle onto tongue.

INACTIVE INGREDIENT

Inactive Ingredients: Acacia gum, lactose, magnesium stearate, corn starch, sucrose.

PATIENT COUNSELING INFORMATION

The letters HPUS indicate that the comonents in this product are officially monographed in the Homeopathic Pharmacopoeia of the United States.

All Native Remedies health products are especially formulated by experts in the field of natural health and are manufactured according to the highest pharmaceutical standards for maximum safety and effectiveness. For more information, visit us at www.nativeremedies.com

Distributed by
Native Remedies, LLC
6531 Park of Commerce Blvd.
Suite 160
Boca Raton, FL 33487
Phone: +1.877.289.1235
International: +1.561.999.8857

Contains no artificial flavors or artificial colors. No gluten added.

STORAGE AND HANDLING

Tamper resistant for your protection. Use only if safety seal is intact.